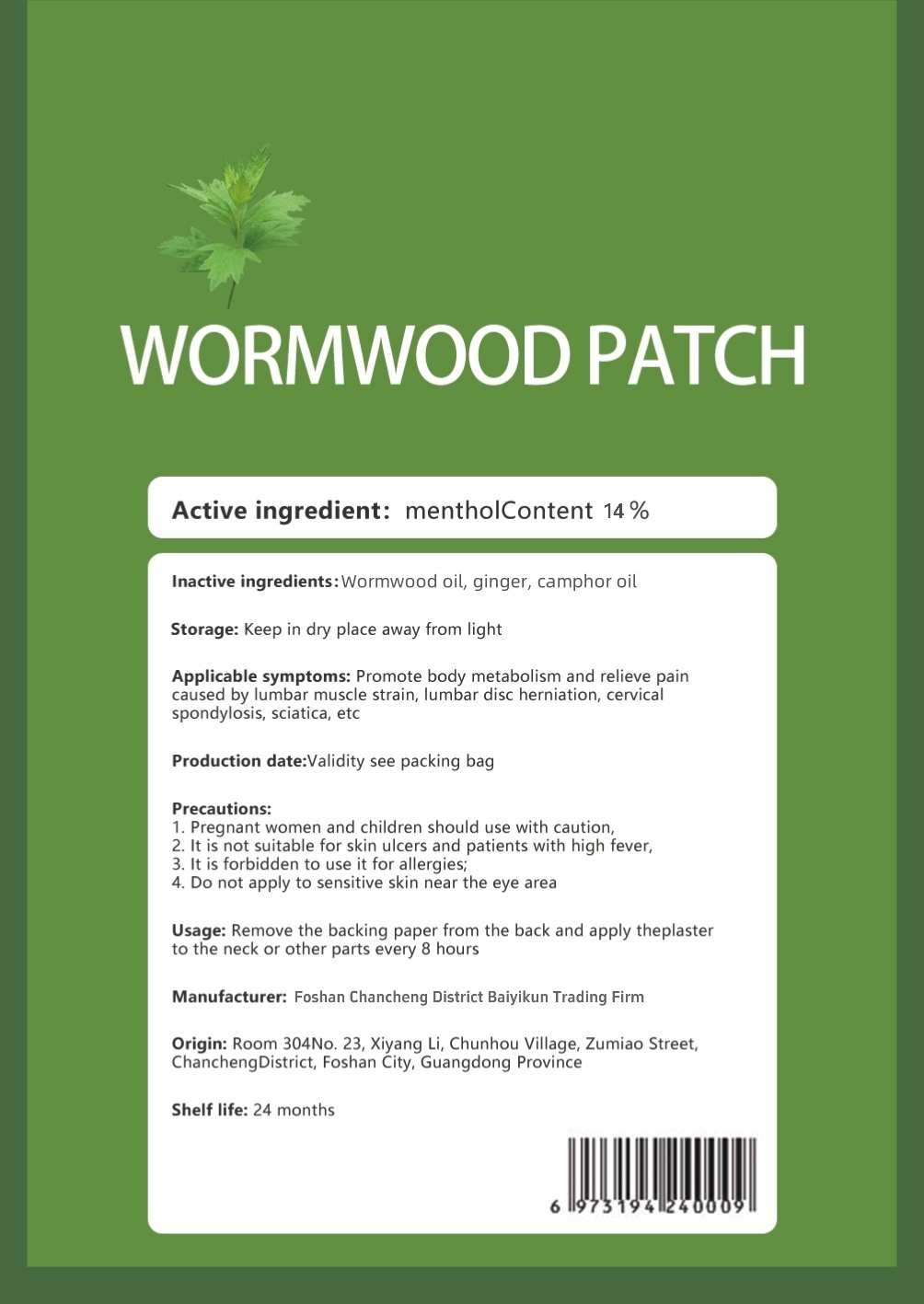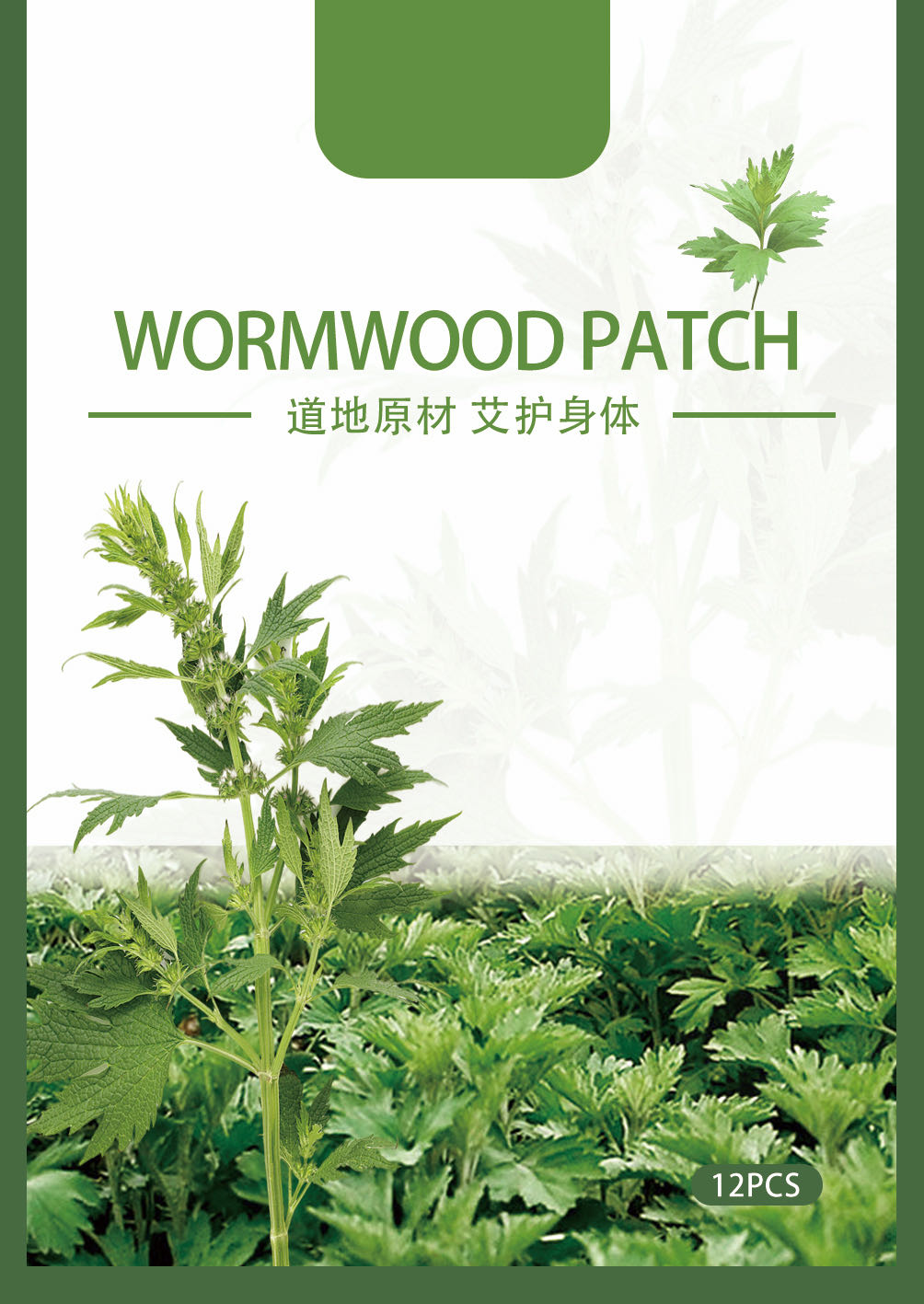 DRUG LABEL: wormwood patch
NDC: 84027-101 | Form: PATCH
Manufacturer: Foshan Chancheng District Baiyikun Trading Firm
Category: otc | Type: HUMAN OTC DRUG LABEL
Date: 20240117

ACTIVE INGREDIENTS: MENTHOL 0.14 g/1 1
INACTIVE INGREDIENTS: GINGER; WORMWOOD OIL; CAMPHOR OIL

wormwood patch

ACTIVE INGREDIENT

menthol 14%

PURPOSE

Applicable symptoms: Promote body metabolism and relieve paincaused by lumbar muscle strain, lumbar disc herniation, cervicalspondylosis, sciatica, etc

Keep out of reach of children

INDICATIONS AND USAGE

Remove the backing paper from the back and apply theplasterto the neck or other parts every 8 hours

WARNINGS

1.Pregnant women and children should use with caution.
2. It is not suitable for skin ulcers and patients with high fever.
3. It is forbidden to use it for allergies.
4. Do not apply to sensitive skin near the eye area.

DOSAGE AND ADMINISTRATION

Remove the backing paper from the back and apply theplasterto the neck or other parts every 8 hours.

Storage: Keep in dry place away from light.

Shelf life: 24 months

INACTIVE INGREDIENT

Wormwood oil, ginger, camphor oil